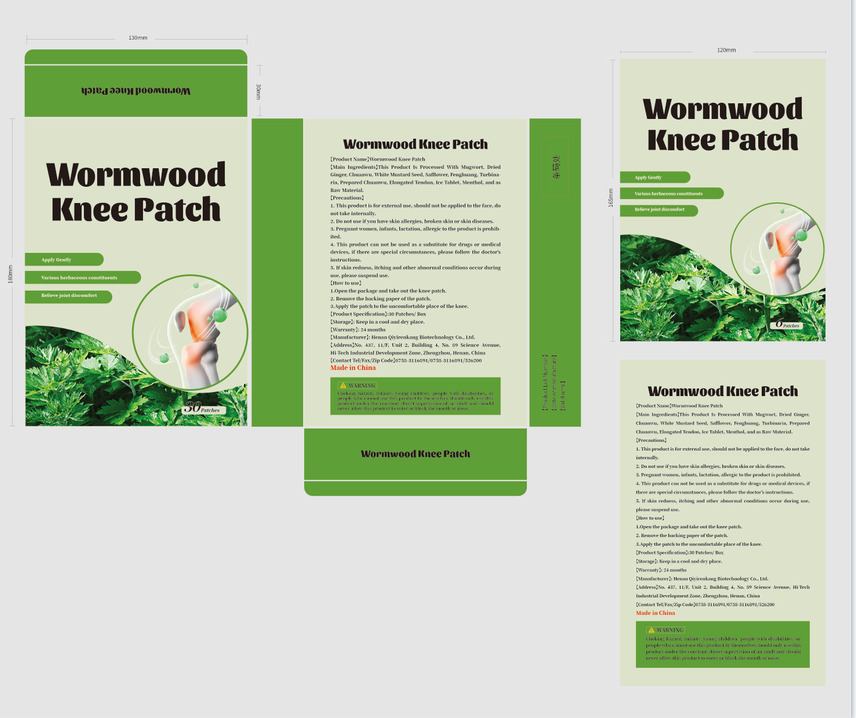 DRUG LABEL: Wormwood Knee Patch
NDC: 84776-003 | Form: CLOTH
Manufacturer: Henan Qiyirenkang Biotechnology Co., Ltd.
Category: otc | Type: HUMAN OTC DRUG LABEL
Date: 20241016

ACTIVE INGREDIENTS: ACONITUM CARMICHAELII WHOLE 0.11 g/100 g; MENTHA CANADENSIS WHOLE 0.06 g/100 g; ARTEMISIA ARGYI WHOLE 0.23 g/100 g; ZINGIBER OFFICINALE WHOLE 0.11 g/100 g; SINAPIS ALBA WHOLE 0.23 g/100 g; DRYOBALANOPS AROMATICA WHOLE 0.06 g/100 g; CARTHAMUS TINCTORIUS WHOLE 0.06 g/100 g
INACTIVE INGREDIENTS: BUTYL ACRYLATE; PETROLATUM; NATURAL LATEX RUBBER

84776-003

Active Ingredient(s)

ARTEMISIA ARGYI WHOLE 0.23%

ZINGIBER OFFICINALE WHOLE 0.11%

ACONITUM CARMICHAELII WHOLE 0.11%

SINAPIS ALBA WHOLE 0.23%

CARTHAMUS TINCTORIUS WHOLE 0.06%

DRYOBALANOPS AROMATICA WHOLE 0.06%

MENTHOL 0.06%

Purpose

Relieve pain

Use

Treating knee pain

Warnings

1. This product is for external use, should not be applied to the face, do not take internally.
2. Do not use if you have skin allergies, broken skin or skin diseases.
3. Pregnant women, infants, lactation, allergic to the product is prohibited.
4. This product can not be uised as a substitute for drugs or medical devices, if there are special circumstances, please follow the doctor's instructions.
5. If skin redness, itching and other abnormal conditions occur during use, please suspend use.

Do not use

Do not using children less than 2 months of age on open skin wounds.

WHEN USING

If skin redness, itching and other abnormal conditions occur during use, please suspend use.

Keep out of reach of children. If swallowed, get medical help or contact a Poison Control Center right away.

Directions

1.Open the package and take out the knee patch.
2. Remove the backing paper of the patch.
3.Apply the patch to the uncomfortable place of the knee.

Other information

【Storage and transport conditions】placed in a ventilated dry place.

Inactive ingredients

BUTYL ACRYLATE, NATURAL LATEX RUBBER , PETROLATUM